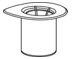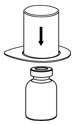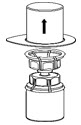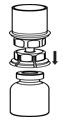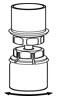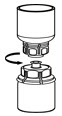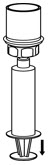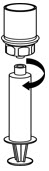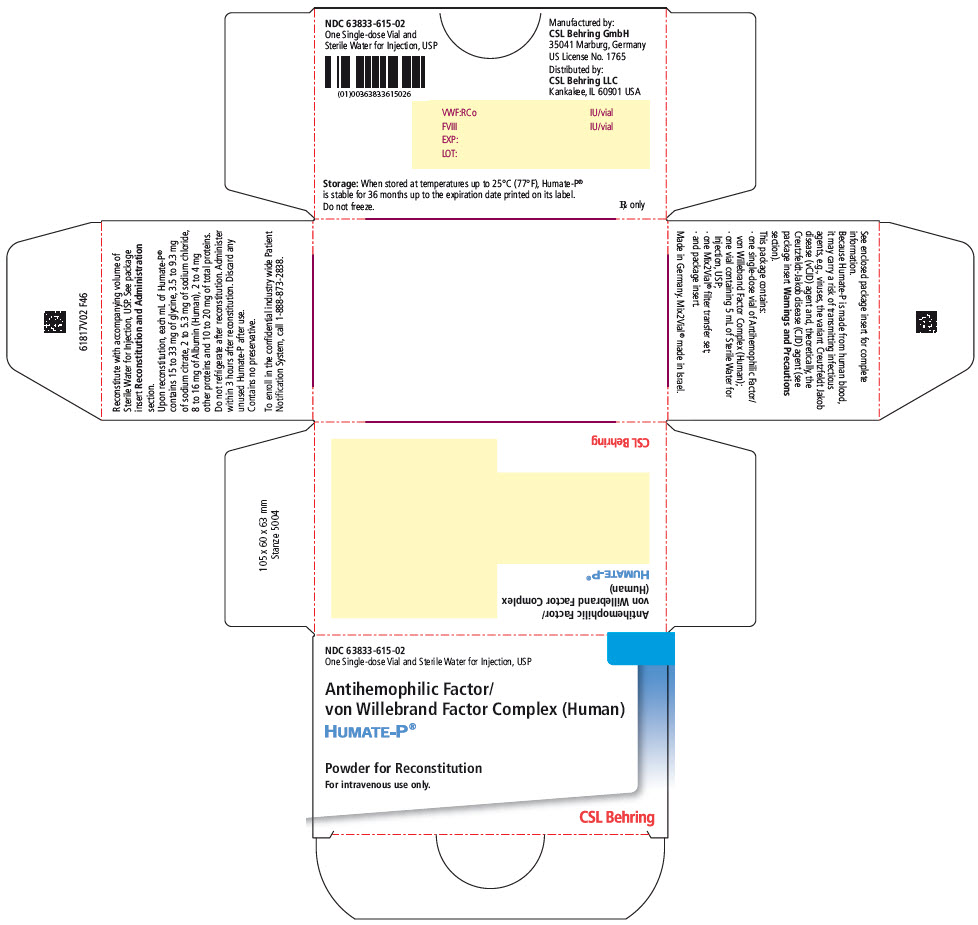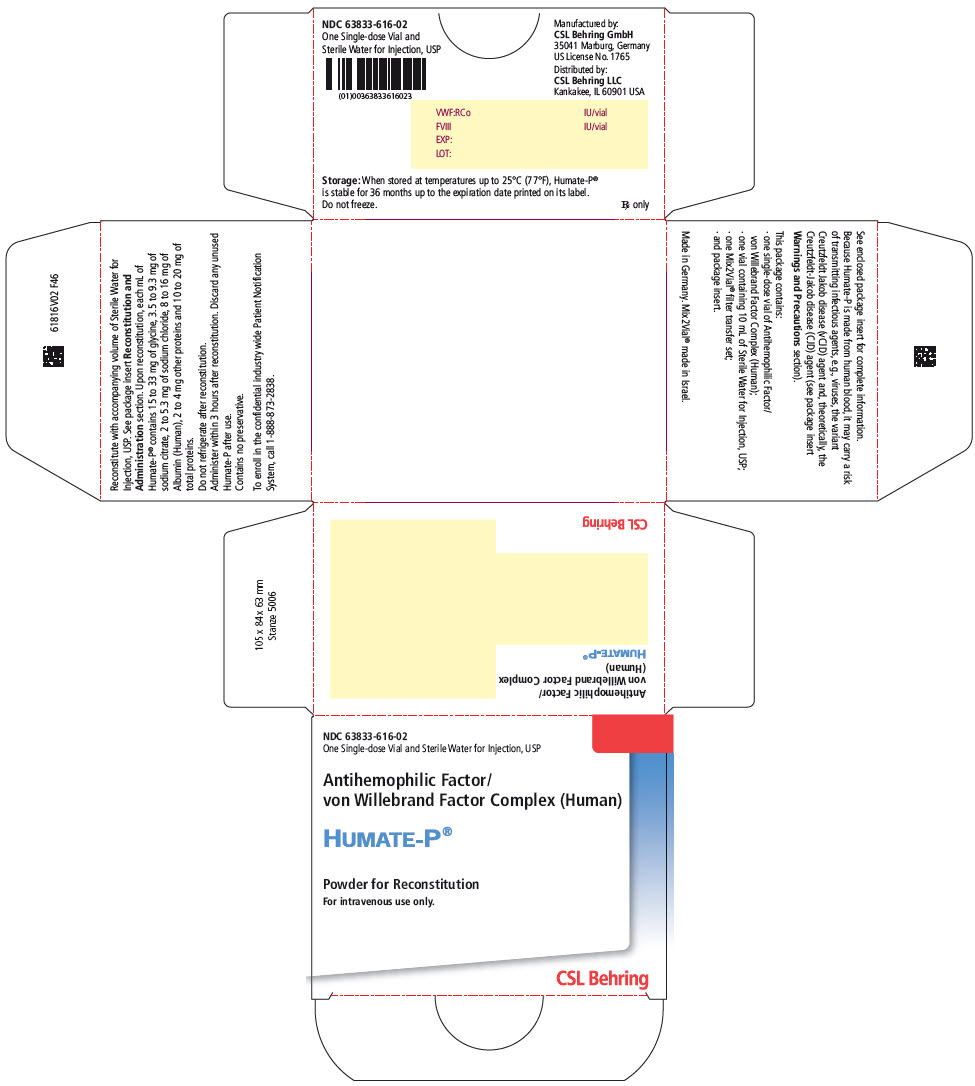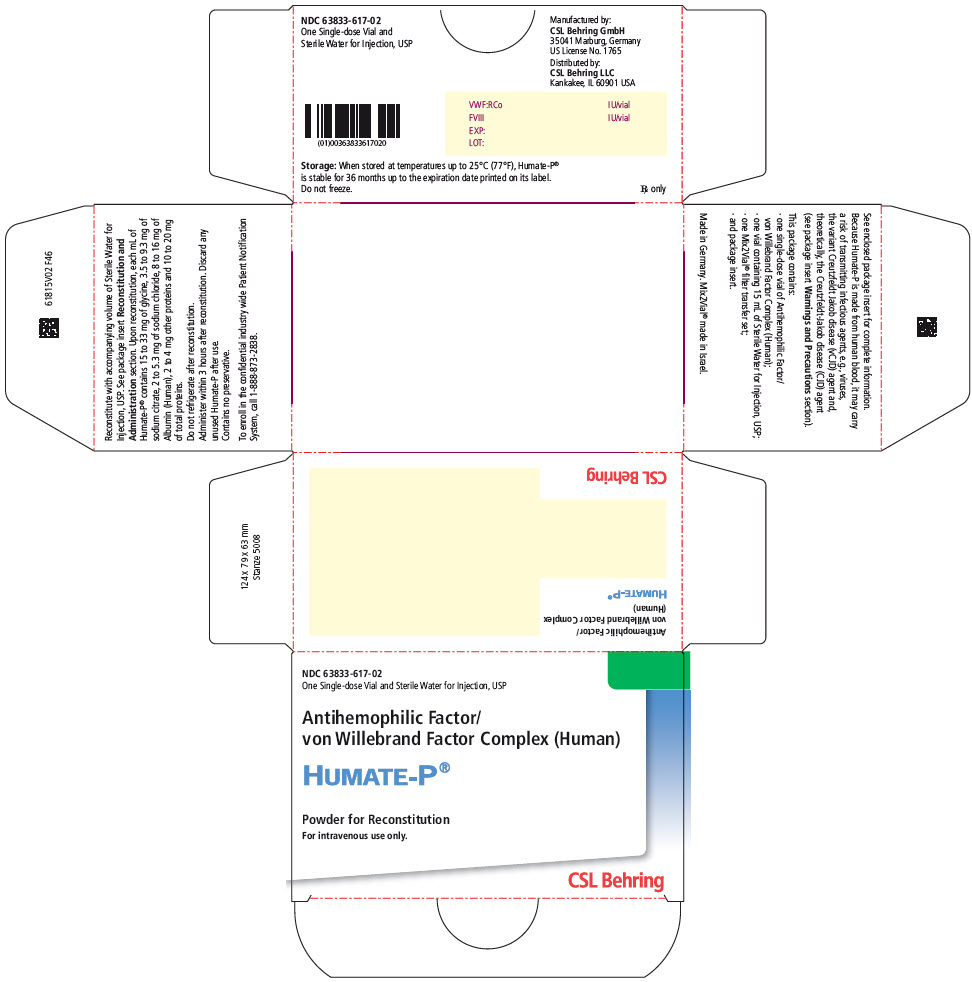 DRUG LABEL: Humate-P
NDC: 63833-615 | Form: KIT | Route: INTRAVENOUS
Manufacturer: CSL Behring GmbH
Category: other | Type: PLASMA DERIVATIVE
Date: 20200817

ACTIVE INGREDIENTS: HUMAN COAGULATION FACTOR VIII/VON WILLEBRAND FACTOR COMPLEX 80 [iU]/1 mL
INACTIVE INGREDIENTS: Glycine 33 mg/1 mL; Sodium Citrate, Unspecified Form 9.3 mg/1 mL; Sodium Chloride 5.3 mg/1 mL; albumin human 16 mg/1 mL; Water

HIGHLIGHTS OF PRESCRIBING INFORMATION

These highlights do not include all the information needed to use
HUMATE-P safely and effectively. See full prescribing information for HUMATE-P.
HUMATE-P [Antihemophilic Factor/von Willebrand Factor Complex (Human)]
Lyophilized Powder for Reconstitution for Intravenous Use Only.
Initial U.S. Approval: 1986

1 INDICATIONS AND USAGE

HUMATE-P is an Antihemophilic Factor/von Willebrand Factor (VWF) Complex (Human) indicated for:

- Hemophilia A – Treatment and prevention of bleeding in adults. (1.1)
- Von Willebrand disease (VWD) – in adults and pediatric patients in the (1) Treatment of spontaneous and trauma-induced bleeding episodes, and (2) Prevention of excessive bleeding during and after surgery. This applies to patients with severe VWD as well as patients with mild to moderate VWD where the use of desmopressin is known or suspected to be inadequate. (1.2) HUMATE-P is not indicated for the prophylaxis of spontaneous bleeding episodes in VWD.

2 DOSAGE AND ADMINISTRATION

For intravenous use only.

Hemophilia A

- One International Unit (IU) of factor VIII (FVIII) activity per kg body weight increases the circulating FVIII level by approximately 2.0 IU/dL. Individualize dosage based on the patient's weight, type and severity of hemorrhage, FVIII level, and presence of inhibitors. (2.1)

VWD

- Treatment of bleeding episodes – 40-80 IU VWF:Ristocetin Cofactor (RCo) per kg body weight (BW) every 8-12 hours. (2.2)
- Prevention of excessive bleeding during and after surgery for all types of VWD. (2.3)

Type of Surgery (see Table 3 for complete surgical dosing) | Calculation of Loading Dose Initial maintenance dose should be half the loading dose (see Table 4 for monitoring recommendations).
Major Surgery (2.3) | Δ [Δ = Target peak plasma VWF:RCo level – baseline plasma VWF:RCo level.] VWF:RCo × BW (kg) IVR [IVR = in vivo recovery as measured in the patient. If the IVR is unknown, use 2.0 IU/dL per IU/kg.] | = IU VWF:RCo required
Minor/Oral Surgery [Oral surgery is defined as extraction of fewer than three teeth, if the teeth are non-molars and have no bony involvement.] (2.3) | Δ VWF:RCo × BW (kg) IVR | = IU VWF:RCo required
Emergency Surgery (2.3) | Administer a dose of 50-60 IU VWF:RCo/kg BW

3 DOSAGE FORMS AND STRENGTHS

HUMATE-P is available as a lyophilized powder in single-dose vials that contain the labeled amount of VWF:RCo and FVIII activity expressed in IU. The average ratio of VWF:RCo to FVIII is 2.4:1. Approximate potencies are shown below: (3)

VWF:RCo/vial | FVIII/vial | Diluent
600 IU | 250 IU | 5 mL
1200 IU | 500 IU | 10 mL
2400 IU | 1000 IU | 15 mL

4 CONTRAINDICATIONS

Anaphylactic or severe systemic reaction to antihemophilic factor or VWF preparations. (4)

5 WARNINGS AND PRECAUTIONS

- VWD patients receiving HUMATE-P may be at risk of developing thromboembolic events. (5.1)
- Monitor for intravascular hemolysis and decreasing hematocrit values in patients with A, B, and AB blood groups who are receiving large or frequent doses. (5.2)
- Monitor VWF:RCo and FVIII levels in VWD patients, especially those undergoing surgery. (5.3)
- Products made from human blood may contain infectious agents (e.g., viruses, the variant Creutzfeldt-Jakob disease (vCJD) agent and, theoretically, the Creutzfeldt-Jakob disease (CJD) agent. (5.4)

6 ADVERSE REACTIONS

Most common adverse reactions observed by >5% of subjects after receiving HUMATE-P are allergic-anaphylactic reactions (e.g., urticaria, chest tightness, rash, pruritus, edema) and, in patients undergoing surgery, postoperative wound and injection-site bleeding, and epistaxis. (6)

To report SUSPECTED ADVERSE REACTIONS, contact CSL Behring Pharmacovigilance at 1-866-915-6958 or FDA at 1-800-FDA-1088 or www.fda.gov/medwatch.

8 USE IN SPECIFIC POPULATIONS

- Pregnancy: No human or animal data. Use only if clearly needed. (8.1)
- The hemostatic efficacy of HUMATE-P has been studied in 34 pediatric subjects with VWD. (8.4) Based on the data from a subset of these subjects, age had no effect on the pharmacokinetics of VWF:RCo. (12.3)

FULL PRESCRIBING INFORMATION

1 INDICATIONS AND USAGE

1.1 Hemophilia A

HUMATE-P, Antihemophilic Factor/von Willebrand Factor Complex (Human), is indicated for treatment and prevention of bleeding in adults with hemophilia A (classical hemophilia).

1.2 Von Willebrand Disease (VWD)

HUMATE-P is also indicated in adult and pediatric patients with von Willebrand disease (VWD) for:

(1) treatment of spontaneous and trauma-induced bleeding episodes, and
(2) prevention of excessive bleeding during and after surgery. This applies to patients with severe VWD as well as patients with mild to moderate VWD where use of desmopressin (DDAVP) is known or suspected to be inadequate.

Controlled clinical trials to evaluate the safety and efficacy of prophylactic dosing with HUMATE-P to prevent spontaneous bleeding have not been conducted in VWD subjects [see Clinical Studies (14)].

2 DOSAGE AND ADMINISTRATION

2.1 Therapy for Hemophilia A

One International Unit (IU) of Factor VIII (FVIII) activity per kg body weight will increase the circulating FVIII level by approximately 2.0 International Units (IU)/dL. Dosage must be individualized based on the patient's weight, type and severity of hemorrhage, FVIII level, and presence of inhibitors. Judge the adequacy of treatment by clinical effects and, in all cases, adjust doses as needed based on clinical judgment and on frequent monitoring of the patient's FVIII level. Table 1 provides dosing recommendations for the treatment of hemophilia A in adults.

Table 1. Dosing Recommendations for the Treatment of Hemophilia A in Adults^1
Hemorrhagic Event | Dosage (IU FVIII:C/kg Body Weight)
Minor hemorrhage:; - Early joint or muscle bleed - Severe epistaxis | Loading dose 15 IU FVIII:C/kg to achieve a FVIII:C plasma level of approximately 30% of normal; one infusion may be sufficient. If needed, half of the loading dose may be given once or twice daily for 1-2 days.
Moderate hemorrhage:; - Advanced joint or muscle bleed - Neck, tongue, or pharyngeal hematoma (without airway compromise) - Tooth extraction - Severe abdominal pain | Loading dose 25 IU FVIII:C/kg to achieve a FVIII:C plasma level of approximately 50% of normal, followed by 15 IU FVIII:C/kg every 8-12 hours for the first 1-2 days to maintain the FVIII:C plasma level at 30% of normal. Continue the same dose once or twice daily for up to 7 days or until adequate wound healing is achieved.
Life-threatening hemorrhage:; - Major surgery - Gastrointestinal bleeding - Neck, tongue, or pharyngeal hematoma (with potential for airway compromise) - Intracranial, intraabdominal, or intrathoracic bleeding - Fractures | Initially 40-50 IU FVIII:C/kg, followed by 20-25 IU FVIII:C/kg every 8 hours to maintain the FVIII:C plasma level at 80-100% of normal for 7 days. Continue the same dose once or twice daily for another 7 days to maintain the FVIII:C level at 30-50% of normal.
IU = International Units.

2.2 Treatment of Bleeding Episodes in VWD

Administer 40 to 80 International Units (IU) VWF:RCo (corresponding to 17 to 33 International Units (IU) FVIII in HUMATE-P) per kg body weight every 8 to 12 hours. Adjust the dosage based on the extent and location of bleeding. Administer repeat doses as long as needed based on monitoring of appropriate clinical and laboratory measures [see Warnings and Precautions (5.2, 5.3)]. Expected levels of VWF:RCo are based on an expected in vivo recovery (IVR) of 2.0 International Units (IU)/dL rise per International Unit (IU)/kg VWF:RCo administered. The administration of 1 International Unit (IU) of FVIII per kg body weight can be expected to lead to a rise in circulating VWF:RCo of approximately 5 International Units (IU)/dL. Table 2 provides dosing recommendations for adult and pediatric patients [see Use in Specific Populations (8.4)].^2

Table 2. VWF:RCo Dosing Recommendations for the Treatment of Bleeding Episodes by VWD Type
VWD Type | Severity of Hemorrhage | Dosage (IU [IU = International Units.] VWF:RCo/kg Body Weight)
Type 1 VWD – Mild (baseline VWF:RCo activity typically >30%) | Minor (e.g., epistaxis, oral bleeding, menorrhagia) | Typically treatable with desmopressin.
Type 1 VWD – Mild (baseline VWF:RCo activity typically >30%) | Minor (when desmopressin is known or suspected to be inadequate) Major [For major bleeds in all types of VWD where repeated dosing is required, monitor and maintain the patient's FVIII level according to the guidelines for hemophilia A therapy.] (e.g., severe or refractory epistaxis, GI bleeding, CNS trauma, traumatic hemorrhage) | Loading dose 40-60 IU/kg. Then 40-50 IU/kg every 8-12 hours for 3 days to keep the trough level of VWF:RCo >50%. Then 40-50 IU/kg daily for up to 7 days.
Type 1 VWD – Moderate or severe (baseline VWF:RCo typically <30%) | Minor (e.g., epistaxis, oral bleeding, menorrhagia) | 40-50 IU/kg (1 or 2 doses).
Type 1 VWD – Moderate or severe (baseline VWF:RCo typically <30%) | Major (e.g., severe or refractory epistaxis, GI bleeding, CNS trauma, hemarthrosis, traumatic hemorrhage) | Loading dose 50-75 IU/kg. Then 40-60 IU/kg every 8-12 hours for 3 days to keep the trough level of VWF:RCo >50%. Then 40-60 IU/kg daily for up to 7 days.
Type 2 VWD (all variants) and Type 3 VWD | Minor (clinical indications above) | 40-50 IU/kg (1 or 2 doses).
Type 2 VWD (all variants) and Type 3 VWD | Major (clinical indications above) | Loading dose 60-80 IU/kg. Then 40-60 IU/kg every 8-12 hours for 3 days to keep the trough level of VWF:RCo >50%. Then 40-60 IU/kg daily for up to 7 days.

2.3 Prevention of Excessive Bleeding During and After Surgery in VWD

The following information provides guidelines for calculating loading and maintenance doses of HUMATE-P for patients undergoing surgery. However in the case of emergency surgery, administer a loading dose of 50 to 60 International Units (IU) VWF:RCo/kg body weight and, subsequently, closely monitor the patient's trough coagulation factor levels.

Measure incremental IVR and assess plasma VWF:RCo and FVIII:C levels in all patients prior to surgery when possible.

To determine IVR:

1. Measure the baseline plasma VWF:RCo level.
2. Infuse a calculated dose [International Units (IU)/kg] of VWF:RCo product intravenously at "time 0".
3. At "time+30 minutes", measure the plasma VWF:RCo level.

Use the following formula to calculate IVR:

IVR = (Plasma VWF:RCotime+30 min – Plasma VWF:RCobaseline International Units (IU)/dL)
Calculated dose (International Units (IU)/kg)

For example, assuming a baseline VWF:RCo of 30 International Units (IU)/dL at "time 0", a calculated dose of 60 International Units (IU)/kg, and a VWF:RCo of 120 International Units (IU)/dL at "time+30 minutes", the IVR would be 1.5 International Units (IU)/dL per International Units (IU)/kg of VWF:RCo administered.

Loading Dose

Table 3 provides guidelines for calculating the loading dose for adult and pediatric patients based on the target peak plasma VWF:RCo level, the baseline VWF:RCo level, body weight in kilograms, and IVR. When individual recovery values are not available, a standardized loading dose can be used based on an assumed VWF:RCo IVR of 2.0 International Units (IU)/dL per International Unit (IU)/kg of VWF:RCo administered.

Table 3. VWF:RCo and FVIII:C Loading Dose Calculations for the Prevention of Excessive Bleeding During and After Surgery for All Types of VWD
Type of Surgery | VWF:RCo Target Peak Plasma Level | FVIII:C Target Peak Plasma Level | Calculation of Loading Dose (to be administered 1 to 2 hours before surgery)
Major | 100 IU/dL | 80-100 IU/dL | Δ [Δ = Target peak plasma VWF:RCo level – baseline plasma VWF:RCo level.] VWF:RCo × BW (kg) IVR [IVR = in vivo recovery as measured in the patient.] | = IU VWF:RCo required
 |  |  | If the IVR is not available, assume an IVR of 2.0 IU/dL per IU/kg and calculate the loading dose as follows: (100 – baseline plasma VWF:RCo) × BW (kg)/2.0
Minor/Oral [Oral surgery is defined as extraction of fewer than three teeth, if the teeth are non-molars and have no bony involvement. Extraction of more than one impacted wisdom tooth is considered major surgery due to the expected difficulty of the surgery and the expected blood loss, particularly in subjects with type 2A or type 3 VWD. Extraction of more than two teeth is considered major surgery in all patients.] | 50-60 IU/dL | 40-50 IU/dL | Δ VWF:RCo × BW (kg) IVR | = IU VWF:RCo required
Emergency | 100 IU/dL | 80-100 IU/dL | Administer a dose of 50-60 IU VWF:RCo/kg body weight.
IU = International Units.
BW = body weight.

For example, the loading dose of HUMATE-P required assuming a target VWF:RCo level of 100 International Units (IU)/dL, a baseline VWF:RCo level of 20 International Units (IU)/dL, an IVR of 2.0 International Units (IU)/dL per International Units (IU)/kg, and a body weight of 70 kg would be 2,800 International Units (IU) VWF:RCo, calculated as follows:

(100 IU/dL – 20 IU/dL) × 70 kg | = 2,800 IU VWF:RCo required
2.0 (IU/dL)/(IU/kg) | = 2,800 IU VWF:RCo required
IU = International Units.

Attaining a target peak FVIII:C plasma level of 80 to 100 International Units (IU) FVIII:C/dL for major surgery and 40 to 50 International Units (IU) FVIII:C/dL for minor surgery or oral surgery might require additional dosing with HUMATE-P. Because the ratio of VWF:RCo to FVIII:C activity in HUMATE-P is 2.4:1, any additional dosing will increase VWF:RCo proportionally more than FVIII:C. Assuming an incremental IVR of 2.0 International Units (IU) VWF:RCo/dL per International Units (IU)/kg infused, additional dosing to increase FVIII:C in plasma will also increase plasma VWF:RCo by approximately 5 International Units (IU)/dL for each International Unit (IU)/kg of FVIII administered.

Maintenance Doses

The initial maintenance dose of HUMATE-P for the prevention of excessive bleeding during and after surgery should be half of the loading dose, irrespective of additional dosing required to meet FVIII:C targets. Subsequent maintenance doses should be based on the patient's VWF:RCo and FVIII levels. Table 4 provides recommendations for target trough plasma levels (based on type of surgery and number of days following surgery) and minimum duration of treatment for subsequent maintenance doses. These recommendations apply to both adult and pediatric patients.

Table 4. VWF:RCo and FVIII:C Target Trough Plasma Level and Minimum Duration of Treatment Recommendations for Subsequent Maintenance Doses for the Prevention of Excessive Bleeding During and After Surgery
Type of Surgery | VWF:RCo Target Trough Plasma Level [Trough levels for either coagulation factor should not exceed 100 IU/dL.] |  | FVIII:C Target Trough Plasma Level |  | Minimum Duration of Treatment
Type of Surgery | Up to 3 days following surgery | After Day 3 | Up to 3 days following surgery | After Day 3 | Minimum Duration of Treatment
Major | >50 IU/dL | >30 IU/dL | >50 IU/dL | >30 IU/dL | 72 hours
Minor | ≥30 IU/dL | – | – | >30 IU/dL | 48 hours
Oral [Oral surgery is defined as extraction of fewer than three teeth, if the teeth are non-molars and have no bony involvement. Extraction of more than one impacted wisdom tooth is considered major surgery due to the expected difficulty of the surgery and the expected blood loss, particularly in subjects with type 2A or type 3 VWD. Extraction of more than two teeth is considered major surgery in all patients.] | ≥30 IU/dL | – | – | >30 IU/dL | 8-12 hours [Administer at least one maintenance dose following oral surgery based on individual pharmacokinetic values. Subsequent therapy with an antifibrinolytic agent is usually administered until adequate healing is achieved.]
IU = International Units.

Based on individual pharmacokinetic-derived half-lives, the frequency of maintenance doses is generally every 8 or 12 hours; patients with shorter half-lives may require dosing every 6 hours. In the absence of pharmacokinetic data, it is recommended that HUMATE-P be administered initially every 8 hours with further adjustments determined by monitoring trough coagulation factor levels. When hemostatic levels are judged insufficient or trough levels are outside the recommended range, consider modifying the administration interval and/or the dose.

It is advisable to monitor trough VWF:RCo and FVIII:C levels at least once a day in order to adjust HUMATE-P dosing as needed to avoid excessive accumulation of coagulation factors. The duration of treatment generally depends on the type of surgery performed, but must be assessed for individual patients based on their hemostatic response [see Clinical Studies (14.2)].

2.4 Reconstitution

- Prepare and administer using aseptic techniques.
- Use either the Mix2Vial® filter transfer set provided with HUMATE-P [see How Supplied/Storage and Handling (16)] or a commercially available double-ended needle and vented filter spike.
- Use plastic disposable syringes with HUMATE-P. Protein solutions of this type tend to adhere to the ground glass surface of all-glass syringes.
- Reconstitute HUMATE-P at room temperature as follows:

1. Ensure that the HUMATE-P vial and diluent vial are at room temperature.
2. Place the HUMATE-P vial, diluent vial and Mix2Vial transfer set on a flat surface.
3. Remove the HUMATE-P and diluent vial flip caps. Wipe the stoppers with an alcohol swab and allow the stoppers to dry prior to opening the Mix2Vial transfer set package.
4. Open the Mix2Vial transfer set package by peeling away the lid (Fig. 1). Leave the Mix2Vial transfer set in the clear package.
  Fig. 1
5. Place the diluent vial on a flat surface and hold the vial tightly. Grip the Mix2Vial transfer set together with the clear package and push the plastic spike at the blue end of the Mix2Vial transfer set firmly through the center of the stopper of the diluent vial (Fig. 2).
  Fig. 2
6. Carefully remove the clear package from the Mix2Vial transfer set. Make sure that you pull up only the clear package, not the Mix2Vial transfer set (Fig. 3).
  Fig. 3
7. With the HUMATE-P vial placed firmly on a flat surface, invert the diluent vial with the Mix2Vial transfer set attached and push the plastic spike of the transparent adapter firmly through the center of the stopper of the HUMATE-P vial (Fig. 4). The diluent will automatically transfer into the HUMATE-P vial.
  Fig. 4
8. With the diluent and Humate-P vial still attached to the Mix2Vial transfer set, gently swirl the HUMATE-P vial to ensure that the HUMATE-P is fully dissolved (Fig. 5). Do not shake the vial.
  Fig. 5
9. With one hand grasp the HUMATE-P side of the Mix2Vial transfer set and with the other hand grasp the blue diluent-side of the Mix2Vial transfer set, and unscrew the set into two pieces (Fig. 6).
  Fig. 6
10. Draw air into an empty, sterile syringe. While the HUMATE-P vial is upright, screw the syringe to the Mix2Vial transfer set. Inject air into the HUMATE-P vial. While keeping the syringe plunger pressed, invert the system upside down and draw the concentrate into the syringe by pulling the plunger back slowly (Fig. 7).
  Fig. 7
11. Now that the concentrate has been transferred into the syringe, firmly grasp the barrel of the syringe (keeping the syringe plunger facing down) and unscrew the syringe from the Mix2Vial transfer set (Fig. 8). Attach the syringe to a suitable intravenous administration set.
  Fig. 8
12. If patient requires more than one vial, pool the contents of multiple vials into one syringe. Use a separate unused Mix2Vial for each product vial.

2.5 Administration

HUMATE-P is for intravenous use only.

- The solution should be clear or slightly opalescent. After filtering/withdrawal, the reconstituted product should be inspected visually for particulate matter and discoloration prior to administration. Even if the directions for use for the reconstitution procedure are precisely followed, it is not uncommon for a few flakes or particles to remain. The filter included in the Mix2Vial device removes those particles completely. Filtration does not influence dosage calculations. Do not use visibly cloudy solutions or solutions still containing flakes or particles after filtration.
- Do not refrigerate HUMATE-P after reconstitution. Administer within 3 hours after reconstitution.
- Slowly infuse the solution (maximally 4 mL/minute) with a suitable intravenous administration set.
- Discard the administration equipment and any unused HUMATE-P after use.

3 DOSAGE FORMS AND STRENGTHS

HUMATE-P is available as a sterile, lyophilized powder for intravenous administration following reconstitution. Each single-dose vial of HUMATE-P contains the labeled amount of VWF:RCo and FVIII activity expressed in International Units (IU). The average ratio of VWF:RCo to FVIII is 2.4:1.

Approximate potencies are shown below; check each carton/vial for the actual potency prior to reconstitution:

Table 5. Dosage Forms and Strengths
VWF:RCo/vial | FVIII/vial | Diluent
600 IU | 250 IU | 5 mL
1200 IU | 500 IU | 10 mL
2400 IU | 1000 IU | 15 mL
IU = International Units.

4 CONTRAINDICATIONS

HUMATE-P is contraindicated in individuals who have had an anaphylactic or severe systemic reaction to antihemophilic factor or von Willebrand factor preparations.

5 WARNINGS AND PRECAUTIONS

5.1 Thromboembolic Events (VWD Patients)

Thromboembolic events have been reported in VWD patients receiving Antihemophilic Factor/von Willebrand Factor Complex replacement therapy, especially in the setting of known risk factors for thrombosis.^3,4 Early reports indicate a higher incidence may occur in females. Endogenous high levels of FVIII have also been associated with thrombosis, but no causal relationship has been established. Exercise caution and consider antithrombotic measures in all at-risk VWD patients who are receiving coagulation factor replacement therapy.

5.2 Monitoring for Intravascular Hemolysis

HUMATE-P contains blood group isoagglutinins (anti-A and anti-B). When doses are very large or need to be repeated frequently (for example, when inhibitors are present or when pre- and post-surgical care is involved), monitor patients of blood groups A, B, and AB for signs of intravascular hemolysis and decreasing hematocrit values and treat appropriately.

5.3 Monitoring VWF:RCo and FVIII Levels

Monitor the VWF:RCo and FVIII levels of VWD patients receiving HUMATE-P using standard coagulation tests, especially in cases of surgery. It is advisable to monitor trough VWF:RCo and FVIII:C levels at least once a day in order to adjust the dosage of HUMATE-P as needed to avoid excessive accumulation of coagulation factors [see Dosage and Administration (2.2, 2.3)].

5.4 Transmission of Infectious Agents

Because HUMATE-P is made from human blood, it may carry a risk of transmitting infectious agents, e.g., viruses, the variant Creutzfeldt-Jakob disease (vCJD) agent and, theoretically, the Creutzfeldt-Jakob disease (CJD) agent [see Description (11) and Patient Counseling Information (17)]. The risk that such products will transmit an infectious agent has been reduced by screening plasma donors for prior exposure to certain viruses, by testing for the presence of certain current virus infections, and by inactivating and/or removing certain viruses during manufacturing [see Description (11)].

Despite these measures, such products can still potentially transmit disease. There is also the possibility that unknown infectious agents may be present in such products. Thus the risk of transmission of infectious agents cannot be eliminated completely. Report all infections thought by a physician possibly to have been transmitted by this product to CSL Behring Pharmacovigilance at 1-866-915-6958 or FDA at 1-800-FDA-1088 or www.fda.gov/medwatch.

Some viruses, such as Parvovirus B19 virus (B19V) or hepatitis A (HAV), are particularly difficult to remove or inactivate. B19V may most seriously affect pregnant women and immune-compromised individuals.

Although the overwhelming number of B19V and HAV cases are community acquired, reports of these infections have been associated with the use of some plasma-derived products. Therefore, physicians should be alert to the potential symptoms of B19V and HAV infections [see Patient Counseling Information (17)].

Symptoms of B19V may include low-grade fever, rash, arthralgia, and transient symmetric, nondestructive arthritis. Diagnosis is often established by measuring B19V-specific IgM and IgG antibodies. Symptoms of HAV include low-grade fever, anorexia, nausea, vomiting, fatigue, and jaundice. A diagnosis may be established by measuring specific IgM antibodies.

Physicians should strongly consider administration of hepatitis A and hepatitis B vaccines to individuals receiving plasma derivatives. Potential risks and benefits of vaccination should be weighed by the physician and discussed with the patient.

6 ADVERSE REACTIONS

The most serious adverse reaction observed in patients receiving HUMATE-P is anaphylaxis. Thromboembolic events have also been observed in patients receiving HUMATE-P for the treatment of VWD [see Warnings and Precautions (5.1)]. Reports of thromboembolic events in VWD patients with other thrombotic risk factors receiving coagulation factor replacement therapy have been obtained from spontaneous reports, published literature, and a European clinical study. In some cases, inhibitors to coagulation factors may occur. However, no inhibitor formation was observed in any of the clinical studies.

In patients receiving HUMATE-P in clinical studies for treatment of VWD, the most commonly reported adverse reactions observed by >5% of subjects are allergic-anaphylactic reactions (including urticaria, chest tightness, rash, pruritus, and edema). For patients undergoing surgery, the most common adverse reactions are postoperative wound and injection-site bleeding, and epistaxis.

6.1 Clinical Trials Experience

Because clinical trials are conducted under widely varying conditions, the adverse reaction rates observed cannot be directly compared to rates in other clinical trials and may not reflect the rates observed in practice.

Treatment of Bleeding Episodes in VWD

Allergic symptoms, including allergic reaction, urticaria, chest tightness, rash, pruritus, and edema, were reported in 6 of 97 (6%) subjects in a Canadian retrospective study [see Clinical Studies (14.1)]. Four of 97 (4%) subjects experienced seven adverse events that were considered to have a possible or probable relationship to HUMATE-P. These included chills, phlebitis, vasodilation, paresthesia, pruritus, rash, and urticaria. All were mild in intensity with the exception of a moderate case of pruritus.

In a prospective, open-label safety and efficacy study of HUMATE-P in VWD subjects with serious life- or limb-threatening bleeding or undergoing emergency surgery, seven of 71 (10%) subjects experienced nine adverse reactions. These were one occurrence each of mild vasodilation and mild pruritis; two occurrences of mild paresthesia; and one occurrence each of moderate peripheral edema and extremity pain and severe pseudothrombocytopenia (platelet clumping with a false low reading). HUMATE-P was discontinued in the subject who experienced the peripheral edema and extremity pain.

Prevention of Excessive Bleeding During and After Surgery in VWD

Among the 63 VWD subjects who received HUMATE-P for prevention of excessive bleeding during and after surgery, including one subject who underwent colonoscopy without the planned polypectomy, the most common adverse events were postoperative hemorrhage (35 events in 19 subjects with five subjects experiencing bleeding at up to three different sites), postoperative nausea (15 subjects), and postoperative pain (11 subjects). Table 6 presents the postoperative hemorrhagic adverse events.

Table 6. Hemorrhagic Adverse Events in 63 Surgical Subjects
Adverse Event | Surgical Procedure Category | Number of Subjects/Events | Onset [On = on-therapy; onset while receiving HUMATE-P or within 1 day of completing HUMATE-P administration. Post = post-therapy; onset at least one day after completing HUMATE-P administration.] (Number of Events) |  | Severity (Number of Events)
 |  |  | On | Post | Mild | Mod | Severe
Wound/injection site bleeding | Major | 8/11 | 7 | 4 | 9 | – | 2
Wound/injection site bleeding | Minor | 2/2 | 2 | – | 1 | 1 | –
Wound/injection site bleeding | Oral | 2/6 | – | 6 | 3 | 3 | –
Epistaxis | Major | 4/4 | 2 | 2 | 3 | 1 | –
Epistaxis | Minor | 1/1 | 1 | – | 1 | – | –
Cerebral hemorrhage/subdural hematoma | Major | 1/2 | 2 [Reported as serious adverse events following intracranial surgery.] | – | – | 2 | –
Gastrointestinal bleeding | Major | 1/3 | 3 [Two of these events were reported as serious adverse events following gastrojejunal bypass.] | – | – | 2 | 1
Menorrhagia | Major | 1/1 | 1 [Reported as a serious adverse event requiring hysterectomy following hysteroscopy and dilation and curettage.] | – | – | 1 | –
Groin bleed | Oral | 1/1 | – | 1 | 1 | – | –
Ear bleed | Major | 1/1 | 1 | – | 1 | – | –
Hemoptysis | Major | 1/1 | 1 | – | 1 | – | –
Hematuria | Major | 1/1 | 1 | – | 1 | – | –
Shoulder bleed | Major | 1/1 | 1 | – | 1 | – | –

Table 7 lists the non-hemorrhagic adverse events reported in at least two subjects, regardless of causality, and the adverse events that were possibly related to HUMATE-P. Pulmonary embolus considered possibly related to HUMATE-P occurred in one elderly subject who underwent bilateral knee replacement.

Table 7. Non-Hemorrhagic and Possibly Related Adverse Events in 63 Surgical Subjects
Body System | Adverse Event (AE) | Number of Subjects with an AE Possibly Related to HUMATE-P | Number of Subjects with an AE Regardless of Causality [Events occurring in two or more subjects.]
Body as a whole | Pain | – | 11
Body as a whole | Fever | – | 4
Body as a whole | Abdominal pain | – | 3
Body as a whole | Infection | – | 3
Body as a whole | Surgery | – | 3
Body as a whole | Back pain | – | 2
Body as a whole | Facial edema | – | 2
Cardiovascular | Chest pain | – | 3
Cardiovascular | Pulmonary embolus [Events occurring in separate subjects.] | 1 | 1
Cardiovascular | Thrombophlebitis | 1 | 1
Digestive | Nausea | 1 | 15
Digestive | Constipation | – | 7
Digestive | Vomiting | 1 | 3
Digestive | Sore throat | – | 2
Hemic and lymphatic system | Anemia/decreased hemoglobin | – | 2
Metabolic/nutritional | Increased SGPT | 1 | 1
Nervous | Dizziness | 1 | 5
Nervous | Headache | 1 | 4
Nervous | Increased sweating | – | 3
Nervous | Insomnia | – | 2
Skin and appendages | Pruritus | – | 3
Skin and appendages | Rash | 1 | 1
Urogenital | Urinary retention | – | 4
Urogenital | Urinary tract infection | – | 2

Eight subjects experienced 10 postoperative serious adverse events: one with subdural hematoma and intracerebral bleeding following intracranial surgery related to an underlying cerebrovascular abnormality; one with two occurrences of gastrointestinal bleeding following gastrojejunal bypass; and one each with sepsis, facial edema, infection, menorrhagia requiring hysterectomy following hysteroscopy and dilation and curettage, pyelonephritis, and pulmonary embolus.

6.2 Postmarketing Experience

The following adverse reactions have been identified during postapproval use of HUMATE-P. Because these reactions are reported voluntarily from a population of uncertain size, it is not always possible to reliably estimate their frequency or establish a causal relationship to HUMATE-P exposure.

Adverse reactions reported in patients receiving HUMATE-P for treatment of VWD or hemophilia A are allergic-anaphylactic reactions (including urticaria, chest tightness, rash, pruritus, edema, and shock), development of inhibitors to FVIII, and hemolysis. Additional adverse reactions reported for VWD are thromboembolic complications, chills and fever, and hypervolemia.

7 DRUG INTERACTIONS

None reported.

8 USE IN SPECIFIC POPULATIONS

8.1 Pregnancy

Animal reproduction studies have not been conducted with HUMATE-P. It is also not known whether HUMATE-P can cause fetal harm when administered to a pregnant woman or can affect reproduction capacity. HUMATE-P should be given to a pregnant woman only if clearly needed.

8.2 Labor and Delivery

It is not known whether HUMATE-P can cause harm to the mother or the fetus when administered during labor and delivery. HUMATE-P should be given during labor and delivery only if clearly needed.

8.3 Nursing Mothers

It is not known whether this drug is excreted in human milk. Because many drugs are excreted in human milk, caution should be exercised when HUMATE-P is administered to a nursing woman.

8.4 Pediatric Use

Hemophilia A

Adequate and well-controlled studies with long-term evaluation of joint damage have not been done in pediatric subjects. Joint damage may result from suboptimal treatment of hemarthroses.

VWD

The safety and effectiveness of HUMATE-P for the treatment of VWD was demonstrated in 26 pediatric subjects, including infants, children, and adolescents, but have not been evaluated in neonates. The safety of HUMATE-P for the prevention of excessive bleeding during and after surgery was demonstrated in eight pediatric subjects (ages 3 to 15) with VWD. Of the 34 pediatric subjects studied for either treatment of bleeding episodes in VWD or prevention of excessive bleeding during and after surgery, four were infants (1 month to under 2 years of age), 23 were children (2 through 12 years), and seven were adolescents (13 through 15 years).

As in adults, pediatric patients should be dosed based on body weight (kg) [see Dosage and Administration (2.2, 2.3)].

8.5 Geriatric Use

Clinical studies of HUMATE-P did not include sufficient numbers of subjects 65 years of age and older to determine whether they respond differently from younger subjects. As for all patients, dosing for geriatric patients should be appropriate to their overall situation.

11 DESCRIPTION

HUMATE-P, Antihemophilic Factor/von Willebrand Factor Complex (Human), is a purified, sterile, lyophilized concentrate of Factor VIII (FVIII) and von Willebrand Factor (VWF) (Human) for intravenous administration in the treatment of patients with classical hemophilia (hemophilia A) and VWD [see Clinical Pharmacology (12)].

HUMATE-P is purified from the cold insoluble fraction of pooled human plasma. The pooled human plasma used to produce HUMATE-P is collected from licensed facilities in the United States (US). All source plasma used in the manufacture of HUMATE-P is tested by FDA-licensed Nucleic Acid Tests (NAT) for hepatitis C virus (HCV), human immunodeficiency virus-1 (HIV-1), hepatitis A virus (HAV), and hepatitis B virus (HBV) and found to be nonreactive (negative).

Each vial of HUMATE-P contains the labeled amount of von Willebrand Factor:Ristocetin Cofactor (VWF:RCo) and FVIII activity expressed in International Units (IU) [see Dosage Forms and Strengths (3)], as defined by the current international standard established by the World Health Organization. One International Unit (IU) of VWF:RCo or FVIII is approximately equal to the amount of VWF:RCo or FVIII in 1.0 mL of fresh-pooled human plasma. The average ratio of VWF:RCo to FVIII is 2.4:1. Fibrinogen content in HUMATE-P is less than or equal to 0.2 mg/mL. HUMATE-P contains anti-A and anti-B blood group isoagglutinins [see Warnings and Precautions (5.2)].

When reconstituted with the volume of Sterile Water for Injection, USP provided, each mL of HUMATE-P contains 72 to 224 International Units (IU) VWF:RCo activity [This correlates to a VWF:RCo to FVIII activity average ratio of 2.4:1, which is used to calculate the nominal values of VWF:RCo activity and is the average VWF:RCo activity.] , 40 to 80 International Units (IU) FVIII activity, 15 to 33 mg of glycine, 3.5 to 9.3 mg of sodium citrate, 2 to 5.3 mg of sodium chloride, 8 to 16 mg of Albumin (Human), 2 to 4 mg of other proteins, and 10 to 20 mg of total proteins. HUMATE-P contains no preservative.

The manufacturing procedure for HUMATE-P includes multiple processing steps that reduce the risk of virus transmission. The virus inactivation/removal capacity consists of four steps:

- Cryoprecipitation
- Al(OH)3 adsorption, glycine precipitation, and NaCl precipitation, studied in combination
- Heat treatment at 60°C for 10 hours in aqueous solution
- Lyophilization

The total cumulative virus reductions range from 6.0 to ≥11.7 log10 as shown in Table 8.

Table 8. Cumulative Virus Reduction Factors for HUMATE-P
Manufacturing Step | Virus Reduction Factor (log10)
Manufacturing Step | Enveloped Viruses |  |  |  | Non-Enveloped Viruses
Manufacturing Step | HIV-1 | BVDV | PRV | WNV | HAV | CPV | B19V
Cryoprecipitation | ND | ND | 1.6 | ND | ND | 1.9 | ND
Al(OH)3 Adsorption/Glycine Precipitation/NaCl Precipitation | 3.8 | 2.8 | 3.9 | ND | 2.3 | 3.0 | ND
Heat Treatment [At 60°C for 10 hours in aqueous solution.] | ≥6.4 | ≥8.9 | 4.7 | ≥7.8 | 4.2 | 1.1 | ≥3.9 [The virus evaluation studies for B19V employed a novel experimental infectivity assay using a clone of the cell line UT7 that contains erythropoietic progenitor cells; (residual) virus titer was determined using an immunofluorescence-based detection method.]
Lyophilization | ND | ND | ND | ND | 1.3 | ND | ND
Cumulative Virus Reduction [log10] | ≥10.2 | ≥11.7 | 10.2 | NA | 7.8 | 6.0 | NA
HIV-1, human immunodeficiency virus type 1, model for HIV-1 and HIV-2
BVDV, bovine viral diarrhea virus, model for HCV
PRV, pseudorabies virus, model for large enveloped DNA viruses
WNV, West Nile virus
HAV, hepatitis A virus
CPV, canine parvovirus, model for B19V
B19V, human parvovirus B19
ND, not determined
NA, not applicable

12 CLINICAL PHARMACOLOGY

12.1 Mechanism of Action

The active components of HUMATE-P consist of two different noncovalently bound proteins (FVIII and VWF). FVIII is an essential cofactor in activation of factor X, leading ultimately to the formation of thrombin and, subsequently, fibrin. VWF promotes platelet aggregation and platelet adhesion on damaged vascular endothelium; activated platelets interact with clotting proteins to form a clot. VWF also serves as a stabilizing carrier protein for the procoagulant protein FVIII.^5,6 The activity of VWF is measured as VWF:RCo.

12.3 Pharmacokinetics

Hemophilia A

After infusion of HUMATE-P, a rapid increase of plasma FVIII:C is followed by a rapid decrease in activity and, subsequently, a slower rate of decrease in activity. Studies with HUMATE-P in subjects with hemophilia A have demonstrated a mean half-life of 12.2 (range: 8.4 to 17.4) hours.

VWD

The pharmacokinetics of HUMATE-P were studied in 41 subjects in a US study and in 28 subjects in a European study [see Clinical Studies (14.2)]. In both studies, subjects were evaluated in the nonbleeding state prior to a surgical procedure. Table 9 summarizes the pharmacokinetics of HUMATE-P based on these studies. Wide inter-subject variability was observed in pharmacokinetic values obtained from these studies.

Table 9. Pharmacokinetics of HUMATE-P in Two Studies of Subjects in the Non-Bleeding State Prior to Surgery
 | US Study | European Study
Number of subjects | 41 | 28
Type 1 VWD | 16 | 10
Type 2A VWD | 2 | 10
Type 2B VWD | 4 | --
Type 2M VWD | 6 | 1
Type 3 VWD | 13 | 7
Dosage of HUMATE-P | 60 IU VWF:RCo/kg BW | 80 IU VWF:RCo/kg BW
Median terminal half-life of VWF:RCo (range) | 11 hours [Excluding 5 subjects with a half-life exceeding the blood sampling time of 24 or 48 hours.] (3.5-33.6) | 10 hours [Excluding 1 subject with a half-life exceeding the blood sampling time of 48 hours.] (2.8-28.3)
Median clearance (range) | 3.1 mL/hr/kg (1-16.6) | 4.8 mL/hr/kg (2.1-53)
Volume of distribution at steady state (range) | 53 mL/kg (29-141) | 59 mL/kg (32-290)
Median IVR for VWF:RCo activity (range) | 2.4 IU/dL per IU/kg (1.1-4.2) | 1.9 IU/dL per IU/kg (0.6-4.5)
IU = International Units.
BW = body weight.

HUMATE-P has been demonstrated in several studies to contain the high molecular weight multimers of VWF. The presence of a multimeric composition of VWF in HUMATE-P is similar to that found in normal plasma and this component is considered to be important for correcting the coagulation defect in patients with VWD.^7,8

The multimeric patterns of HUMATE-P in the US study were measured in 13 subjects with type 3 VWD; 11 had absent or barely detectable multimers at baseline. Of those 11 subjects, all had some high molecular weight multimers present 24 hours after infusion of HUMATE-P. In the European study, infusion of HUMATE-P corrected the defect of the multimer pattern in subjects with types 2A and 3 VWD. High molecular weight multimers were detectable until at least 8 hours after infusion.

Based on the small sample size evaluation, it appears that age, sex, and type of VWD have no impact on the pharmacokinetics of VWF:RCo.

14 CLINICAL STUDIES

Controlled clinical studies to evaluate the safety and efficacy of prophylactic dosing with HUMATE-P to prevent spontaneous bleeding have not been conducted in VWD subjects. Adequate data are not presently available on which to evaluate or to base dosing recommendations in this setting.

14.1 Treatment of Bleeding Episodes in VWD

Clinical efficacy of HUMATE-P in the control of bleeding in subjects with VWD was determined by a retrospective review of clinical safety and efficacy data obtained from 97 Canadian VWD subjects who received product under an Emergency Drug Release Program. The dosage schedule and duration of therapy were determined by the medical practitioner.

There were 514 requests for product use for surgery, bleeding, or prophylaxis in the 97 subjects. Of these, HUMATE-P was not used in 151 cases, and follow-up safety and/or efficacy information was available for 303 (83%) of the remaining 363 requests. In many cases, HUMATE-P from a single request was used for several treatment courses in one subject. Therefore, there are more reported treatment courses than requests.

HUMATE-P was administered to 97 subjects in 530 treatment courses: 73 for surgery, 344 for treatment of bleeding, and 20 for prophylaxis of bleeding. The majority of the 93 "other" uses involved dental procedures, diagnostic procedures, prophylaxis prior to a procedure, or test doses.

Table 10 summarizes the dosing information (all subjects) for bleeding episodes.

Table 10. Dosing Information for Bleeding Episodes in VWD
 |  | Type/Location of Bleeding Episode
 |  | Digestive System | Nose+Mouth +Pharynx | Integument System | Female Genital System | Musculo-skeletal
No. of Subjects |  | 14 | 29 | 11 | 4 | 22
Loading Dose | Mean Dose (SD) [IU VWF:RCo/kg.] | 62.1 (31.1) | 66.9 (24.3) | 73.4 (37.7) | 88.5 (28.3) | 50.2 (24.9)
 | No. of Infusions [Number of infusions where the dose per kg body weight was available.] | 37 | 127 | 22 | 7 | 107
Maintenance Dose | Mean Dose (SD) | 61.5 (38.0) | 67.5 (22.4) | 56.5 (63.3) | 74.5 (17.7) | 63.8 (28.8)
 | No. of Infusions | 250 | 55 | 4 | 15 | 121
No. of Treatment Days per Bleeding Episode | Mean (SD) No. of Events | 4.6 (3.6) 49 | 1.4 (1.2) 130 | 1.1 (0.4) 22 | 2.8 (2.9) 9 | 2.0 (1.9) 108
No. of Infusions by Treatment Day
No. of Subjects |  | 14 | 29 | 11 | 4 | 22
Day 1 [Day 1, first treatment day.] | Mean (SD) No. of Events | 1.2 (0.4) 49 | 1.1 (0.2) 130 | 1.0 (0.2) 22 | 1.0 (0.0) 9 | 1.0 (0.1) 108
No. of Subjects |  | 13 | 9 | 3 | 1 | 15
Day 2 | Mean (SD) No. of Events | 1.2 (0.6) 41 | 1.3 (0.5) 12 | 1.0 (0.0) 3 | 1.0 (-) 1 | 1.2 (0.5) 26
No. of Subjects |  | 12 | 6 | - | 2 | 10
Day 3 | Mean (SD) No. of Events | 1.5 (0.8) 25 | 1.4 (0.7) 9 | - - | 1.0 (0.0) 3 | 1.2 (0.4) 18
SD, standard deviation.

14.2 Prevention of Excessive Bleeding During and After Surgery in VWD

Two prospective, open-label, non-controlled, multicenter clinical studies, one in the US and one in Europe, investigated the safety and hemostatic efficacy of HUMATE-P in subjects with VWD undergoing surgery.

• US clinical study – The primary objective of this study was to demonstrate the safety and hemostatic efficacy of HUMATE-P in preventing excessive bleeding in adult and pediatric subjects with VWD undergoing surgery. The 35 subjects (21 female and 14 male) ranged in age from 3 to 75 years (mean 32.9); seven were age 15 or younger and two were age 65 or older. Twelve subjects had type 1 VWD, two had type 2A, three had type 2B, five had type 2M, and 13 had type 3. Twenty-eight of the surgical procedures were classified as major (e.g., orthopedic joint replacement, intracranial surgery, multiple tooth extractions, laparoscopic cholecystectomy), four as minor (e.g., placement of intravenous access device), and three subjects had oral surgery [Oral surgery is defined as extraction of fewer than three teeth, if the teeth are non-molars and have no bony involvement. Extraction of more than one impacted wisdom tooth is considered major surgery due to the expected difficulty of the surgery and the expected blood loss, particularly in subjects with type 2A or type 3 VWD. Extraction of more than two teeth is considered major surgery in all patients.] . Seven of the 13 subjects with type 3 VWD had major surgery.

The first 15 subjects received a loading dose of HUMATE-P corresponding to 1.5 times the "full dose" (defined as the dose predicted to achieve a peak VWF:RCo level of 100 International Units (IU)/dL as determined by each subject's calculated IVR and baseline VWF:RCo level); the loading dose did not vary with the type of surgery performed (i.e., major, minor, or oral). The remaining 20 subjects were dosed based on individual pharmacokinetic assessments and target peak VWF:RCo levels of 80 to 100 International Units (IU)/dL for major surgery and 50 to 60 International Units (IU)/dL for minor or oral surgery, respectively. All 35 subjects received initial maintenance doses corresponding to 0.5 times the full dose at intervals of 6, 8, or 12 hours after surgery as determined by their individual half-lives for VWF:RCo; subsequent maintenance doses were adjusted based on regular measurements of trough VWF:RCo and FVIII:C levels. The median duration of treatment was 1 day (range: 1 to 2 days) for oral surgery, 5 days (range: 3 to 7 days) for minor surgery, and 5.5 days (range: 2 to 26 days) for major surgery.

• European clinical study – The primary objective of this study was to assess the ability of HUMATE-P to effectively correct the coagulation defect in subjects with VWD undergoing elective surgery, as demonstrated by an increase in VWF:RCo and FVIII, a shortening of the prolonged bleeding time, and the prevention and/or cessation of excessive bleeding. This study did not have a pre-stated hypothesis to evaluate hemostatic efficacy. The 27 subjects (18 females and nine males) ranged in age from 5 to 81 years (median age: 46 years); one was age 5, and five were older than 65. Ten subjects had type 1 VWD, nine had type 2A, one had type 2M, and seven had type 3. Sixteen of the surgical procedures were classified as major (orthopedic joint replacement, hysterectomy, multiple tooth extractions, laparoscopic adnexectomy, laparoscopic cholecystectomy, and basal cell carcinoma excision). Six of the seven subjects with type 3 VWD had major surgery.

Dosing was individualized based on a pharmacokinetic assessment performed before surgery. The median duration of treatment was 3.5 days (range: 1 to 17 days) for minor surgery and 9 days (range: 1 to 17 days) for major surgery.

In both studies, assessments of the hemostatic efficacy of HUMATE-P in preventing excessive bleeding were performed at the end of surgery, 24 hours after the last infusion of HUMATE-P, and at the end of the study (14 days following surgery).

Table 11 summarizes the end-of-surgery hemostatic efficacy assessments in subjects participating in either the US or European study.

Table 11. Investigator's End-of-Surgery Hemostatic Efficacy Assessments for the US and European Surgical Studies
 | Number of Subjects | End-of-Surgery Hemostatic Efficacy Assessments
 | Number of Subjects | Effective (Excellent / Good) [Excellent: Hemostasis clinically not significantly different from normal. Good: Mildly abnormal hemostasis in terms of quantity and/or quality (e.g., slight oozing).] | 95% Confidence Interval (CI) for Effective Proportion [95% CIs according to Blyth-Still-Casella.]
US study | 35 | 32 (91.4%) | 78.5-97.6%
European study | 26 [One subject with missing information.] | 25 (96%) | 82-99.8%

Table 12 summarizes the overall hemostatic efficacy assessments in subjects participating in either the US or European study. HUMATE-P was effective in preventing excessive bleeding during and after surgery.

Table 12. Investigator's Overall Hemostatic Efficacy Assessments for the US and European Surgical Studies
 | Number of Subjects | Overall Hemostatic Assessments
 | Number of Subjects | Effective (Excellent / Good) [Excellent: Hemostasis clinically not significantly different from normal. Good: Mildly abnormal hemostasis in terms of quantity and/or quality (e.g., slight oozing).] | 95% CI for Effective Proportion [95% CIs according to Blyth-Still-Casella.]
US study [Overall hemostatic efficacy was assessed 24 hours after the last HUMATE-P infusion or 14 days after surgery, whichever came earlier.] | 35 | 35 (100%) | 91.3-100%
European study [Overall hemostatic efficacy was not prospectively defined for the European study; the efficacy result displayed is the least efficacious ranking assigned by an investigator between surgery and Day 14.] | 27 | 26 (96.3%) | 82.5-99.8%

In the US study, all efficacy assessments were reviewed by an independent Data Safety Monitoring Board (DSMB). The DSMB agreed with the investigators' assessments of the overall hemostatic efficacy for all but two subjects (neither of whom had type 3 VWD). Based on this, the DSMB judged hemostatic efficacy as "effective" in 33 (94.3%) (95% CI: 81.1% to 99.0%) of the 35 subjects.

In the US study, the median actual estimated blood loss did not exceed the median expected blood loss, regardless of the type of surgery. Table 13 shows the median expected and actual estimated blood loss during surgery in the US study.

Table 13. Expected and Actual Estimated Blood Loss During Surgery in the US Study
Estimated Blood Loss | Oral Surgery (n=3) | Minor Surgery (n=4) | Major Surgery (n=28) | Total (n=35)
Expected – Median (range) mL | 10 (5-50) | 8 (0-15) | 50 (0-300) [One subject with missing information] | 20 (0-300)
Actual – Median (range) mL | 3 (0-15) | 3 (0-10) | 26 (0-300) [Five subjects with missing information] | 18 (0-300)

In the US study, four subjects received transfusions, three due to adverse events and one due to pre-existing anemia. In the European study, one subject received transfusions to treat pre-existing anemia.

14.3 Virus Transmission Studies

Clinical evidence of the absence of virus transmission in HUMATE-P was obtained in additional studies.

In one study, none of the evaluable subjects (31 of 67) who received HUMATE-P developed HBV infection or showed clinical signs of non-A, non-B (NANB) hepatitis infection.

In another study, 32 lots of HUMATE-P were administered to 26 subjects with hemophilia or VWD who had not previously received any blood products. No subject developed any signs of an infectious disease, and the 10 subjects not previously vaccinated remained seronegative for markers of infection with HBV, HAV, cytomegalovirus (CMV), Epstein-Barr virus, and HIV.

In a retrospective study, 155 subjects evaluated remained negative for the presence of HIV-1 antibodies for time periods ranging from 4 months to 9 years from the initial administration of HUMATE-P. All 67 of the subjects tested for HIV-2 antibodies remained seronegative.

15 REFERENCES

1. Levine PH, Brettler DB. Clinical aspects and therapy for hemophilia A. In: Hoffman R, Benz JB, Shattil SJ, Furie B, Cohen HJ, eds. Hematology: Basic Principles and Practice. New York: Churchill Livingstone Inc.; 1991:1296-1297.
2. Scott JP, Montgomery RT. Therapy of von Willebrand disease. Semin Thromb Hemost. 1993;19:37-47.
3. Mannucci, PM. Venous Thromboembolism in Von Willebrand Disease. Thromb Haemostas. 2002;88:378-379.
4. Markis M, Colvin B, Gupta V, Shields ML, Smith MP. Venous thrombosis following the use of intermediate purity FVIII concentrate to treat patients with von Willebrand's disease. Thromb Haemostas. 2002;88:387-388.
5. Hoyer LW. The factor VIII complex: structure and function. Blood. 1981;58:1-13.
6. Meyer D, Girma J-P. von Willebrand factor: structure and function. Thromb Haemostas. 1993;70:99-104.
7. Berntorp E, Nilsson IM. Biochemical and in vivo properties of commercial virus-inactivated factor VIII concentrates. Eur J Haematol. 1988;40:205-214.
8. Berntorp E. Plasma product treatment in various types of von Willebrand's disease. Haemostasis. 1994;24:289-297.

16 HOW SUPPLIED/STORAGE AND HANDLING

- HUMATE-P is supplied in a single-dose vial containing the labeled amount of VWF:RCo and FVIII activity expressed in International Units (IU).
- Components are not made with natural rubber latex.
- When stored at temperatures up to 25°C (77°F), HUMATE-P is stable for 36 months up to the expiration date printed on its label. Do not freeze.
- HUMATE-P does not contain a preservative and should be used within 3 hours after reconstitution.

STORAGE AND HANDLING

Table 14. How Supplied

Each product presentation includes a package insert and the following components:

Presentation | Carton NDC Number | Components
600 IU VWF:RCo and 250 IU FVIII | 63833-615-02 | - HUMATE-P in a single-dose vial [NDC 63833-625-01] - 5 mL vial of Sterile Water for Injection, USP [NDC 63833-765-53] - Mix2Vial transfer set
1200 IU VWF:RCo and 500 IU FVIII | 63833-616-02 | - HUMATE-P in a single-dose vial [NDC 63833-626-01] - 10 mL vial of Sterile Water for Injection, USP [NDC 63833-765-54] - Mix2Vial transfer set
2400 IU VWF:RCo and 1000 IU FVIII | 63833-617-02 | - HUMATE-P in a single-dose vial [NDC 63833-627-01] - 15 mL vial of Sterile Water for Injection, USP [NDC 63833-765-55] - Mix2Vial transfer set

17 PATIENT COUNSELING INFORMATION

Inform patients that HUMATE-P is made from human plasma (part of the blood) and may contain infectious agents that can cause disease (e.g., viruses, the variant Creutzfeldt-Jakob disease (vCJD) agent and, theoretically, the Creutzfeldt-Jakob (CJD) agent). Explain that the risk that HUMATE-P may transmit an infectious agent has been reduced by screening plasma donors, by testing the donated plasma for certain virus infections, and by inactivating and/or removing certain viruses during manufacturing [see Warnings and Precautions (5.4)].

Inform patients that some viruses, such as B19V and HAV, may be particularly difficult to remove or inactivate. Advise patients, especially pregnant women and immune-compromised individuals, to report low-grade fever, rash, joint pain, anorexia, nausea, vomiting, fatigue, and jaundice [see Warnings and Precautions (5.4)].

Manufactured by:
CSL Behring GmbH
35041 Marburg, Germany
US License No. 1765

Distributed by:
CSL Behring LLC
Kankakee, IL 60901 USA

Mix2Vial® is a registered trademark of West Pharma. Services IL, Ltd., a subsidiary of West Pharmaceutical Services, Inc.

PRINCIPAL DISPLAY PANEL - Kit Carton - NDC 63833-615-02

NDC 63833-615-02
One Single-dose Vial and Sterile Water for Injection, USP

Antihemophilic Factor/
von Willebrand Factor Complex (Human)

HUMATE-P®

Powder for Reconstitution

For intravenous use only.

CSL Behring

PRINCIPAL DISPLAY PANEL - Kit Carton - NDC 63833-616-02

NDC 63833-616-02
One Single-dose Vial and Sterile Water for Injection, USP

Antihemophilic Factor/
von Willebrand Factor Complex (Human)

HUMATE-P®

Powder for Reconstitution

For intravenous use only.

CSL Behring

PRINCIPAL DISPLAY PANEL - Kit Carton - NDC 63833-617-02

NDC 63833-617-02
One Single-dose Vial and Sterile Water for Injection, USP

Antihemophilic Factor/
von Willebrand Factor Complex (Human)

HUMATE-P®

Powder for Reconstitution

For intravenous use only.

CSL Behring